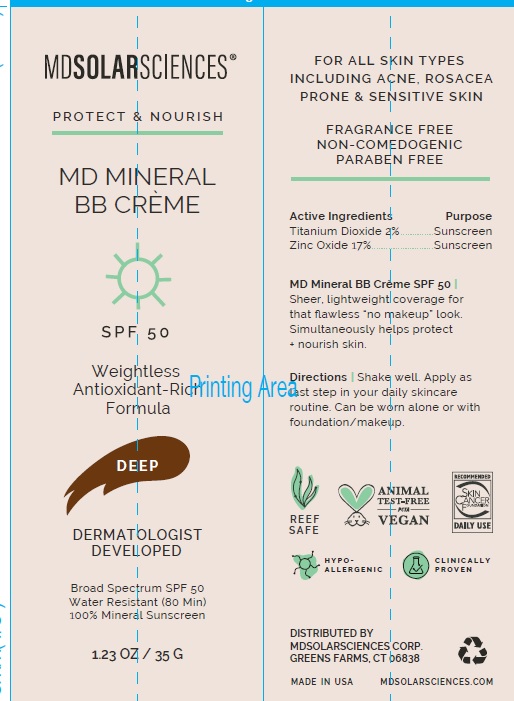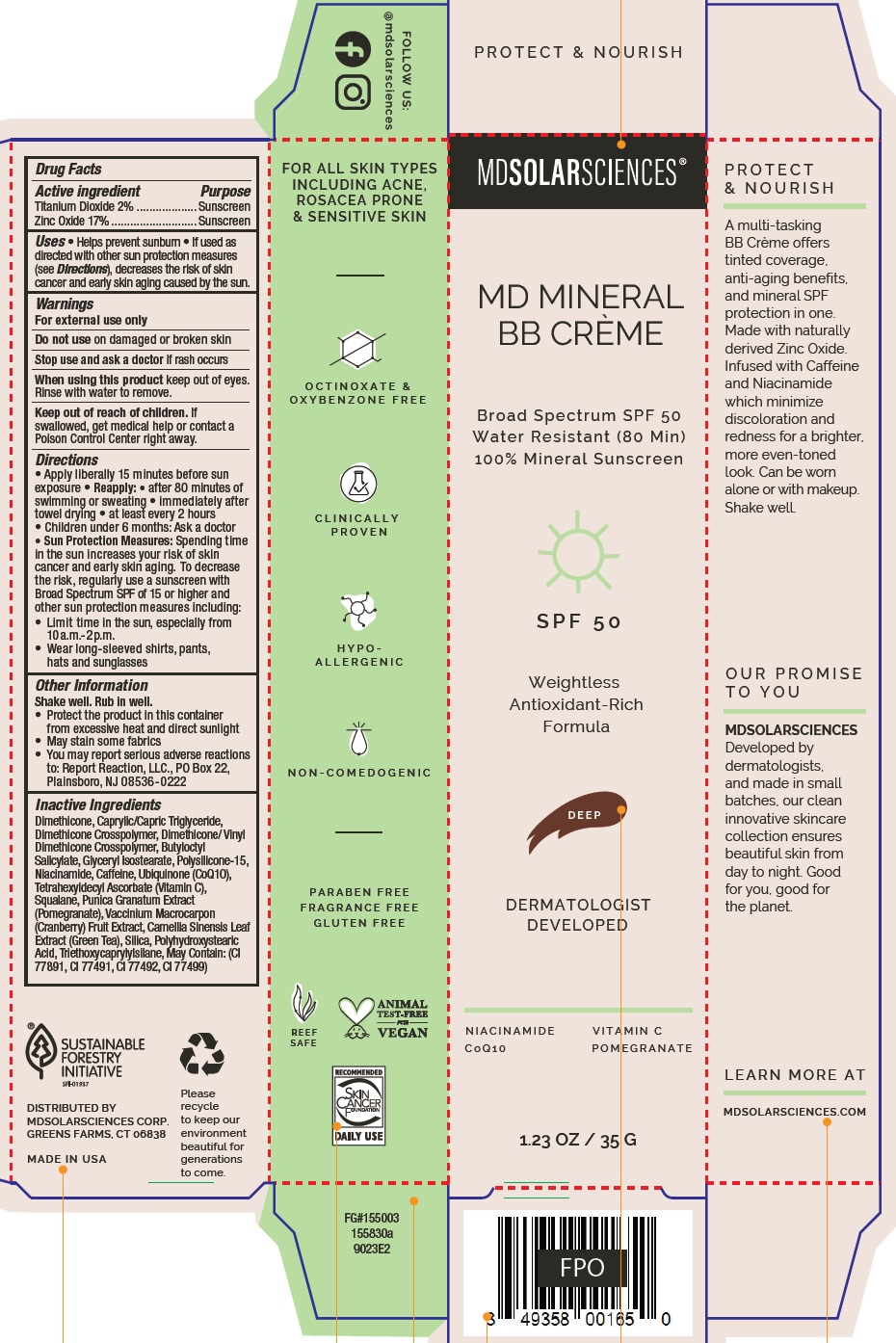 DRUG LABEL: MD Mineral BB Creme Broad Spectrum SPF 50 Water Resistant 80 Min
NDC: 14268-126 | Form: CREAM
Manufacturer: ENGLEWOOD LAB, INC.
Category: otc | Type: HUMAN OTC DRUG LABEL
Date: 20231212

ACTIVE INGREDIENTS: TITANIUM DIOXIDE 20 mg/1 g; ZINC OXIDE 170 mg/1 g
INACTIVE INGREDIENTS: DIMETHICONE; MEDIUM-CHAIN TRIGLYCERIDES; BUTYLOCTYL SALICYLATE; GLYCERYL ISOSTEARATE; POLYSILICONE-15; NIACINAMIDE; CAFFEINE; UBIDECARENONE; TETRAHEXYLDECYL ASCORBATE; SQUALANE; PUNICA GRANATUM ROOT BARK; CRANBERRY; GREEN TEA LEAF; SILICON DIOXIDE; TRIETHOXYCAPRYLYLSILANE

Bass Pro Shops Mineral Sun Stick Sunscreen Broad Spec SPF 40

Active ingredients

Titanium Dioxide 2%.

Zinc Oxide 17%

Purpose

Sunscreen

Uses

• Helps prevent sunburn • If used as directed with other sun protection measures (see), decreases the risk of skin cancer and early skin aging caused by the sun. Directions

Warnings

For external use only

Do not use

on damaged or broken skin

Stop use and ask a doctor

if rash occurs

When using this product

keep out of eyes. Rinse with water to remove.

Keep out of reach of children.

If swallowed, get medical help or contact a Poison Control Center right away.

Directions

• Apply liberally 15 minutes before sun exposure • : • after 80 minutes of swimming or sweating • immediately after towel drying • at least every 2 hours • Children under 6 months: Ask a doctor • Spending time in the sun increases your risk of skin cancer and early skin aging. To decrease the risk, regularly use a sunscreen with Broad Spectrum SPF of 15 or higher and other sun protection measures including: • Limit time in the sun, especially from 10a.m. - 2p.m. • Wear long-sleeved shirts, pants, hats and sunglasses
Reapply Sun Protection Measures:

Other Information

•Protect the product in this container from excessive heat and direct sunlight • May stain some fabrics • You may report serious adverse reactions to: Report Reaction, LLC., PO Box 22, Plainsboro, NJ 08536-0222 Shake well. Rub in well.

Inactive Ingredients

Dimethicone, Caprylic/Capric Triglyceride, Dimethicone Crosspolymer, Dimethicone/ Vinyl Dimethicone Crosspolymer, Butyloctyl Salicylate, Glyceryl Isostearate, Polysilicone-15, Niacinamide, Caffeine, Ubiquinone (CoQ10), Tetrahexyldecyl Ascorbate (Vitamin C), Squalane, Punica Granatum Extract (Pomegranate), Vaccinium Macrocarpon (Cranberry) Fruit Extract, Camellia Sinensis Leaf Extract (Green Tea), Silica, Polyhydroxystearic Acid, Triethoxycaprylylsilane, May Contain: (CI 77891, CI 77491, CI 77492, CI 77499)